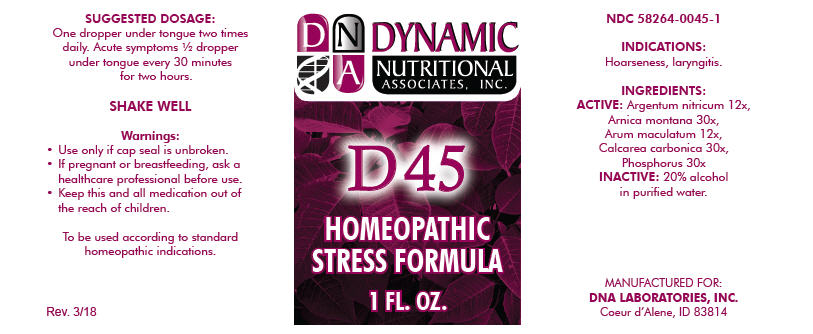 DRUG LABEL: D-45
NDC: 58264-0045 | Form: SOLUTION
Manufacturer: DNA Labs, Inc.
Category: homeopathic | Type: HUMAN OTC DRUG LABEL
Date: 20250113

ACTIVE INGREDIENTS: SILVER NITRATE 12 [hp_X]/1 mL; ARNICA MONTANA 30 [hp_X]/1 mL; ARUM MACULATUM ROOT 12 [hp_X]/1 mL; OYSTER SHELL CALCIUM CARBONATE, CRUDE 30 [hp_X]/1 mL; PHOSPHORUS 30 [hp_X]/1 mL
INACTIVE INGREDIENTS: ALCOHOL; WATER

D-45

NDC 58264-0045-1

INDICATIONS

PURPOSE

Hoarseness, laryngitis.

INGREDIENTS

ACTIVE

Argentum nitricum 12x, Arnica montana 30x, Arum maculatum 12x, Calcarea carbonica 30x, Phosphorus 30x

INACTIVE

20% alcohol in purified water.

SUGGESTED DOSAGE

One dropper under tongue two times daily. Acute symptoms ½ dropper under tongue every 30 minutes for two hours.

STORAGE AND HANDLING

SHAKE WELL

Warnings

- Use only if cap seal is unbroken.

PREGNANCY OR BREAST FEEDING

- If pregnant or breastfeeding, ask a healthcare professional before use.

KEEP OUT OF REACH OF CHILDREN

- Keep this and all medication out of the reach of children.

To be used according to standard homeopathic indications.

PRINCIPAL DISPLAY PANEL - 1 FL. OZ. Bottle Label

DYNAMIC
NUTRITIONAL
ASSOCIATES, INC.

D 45

HOMEOPATHIC
STRESS FORMULA

1 FL. OZ.